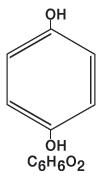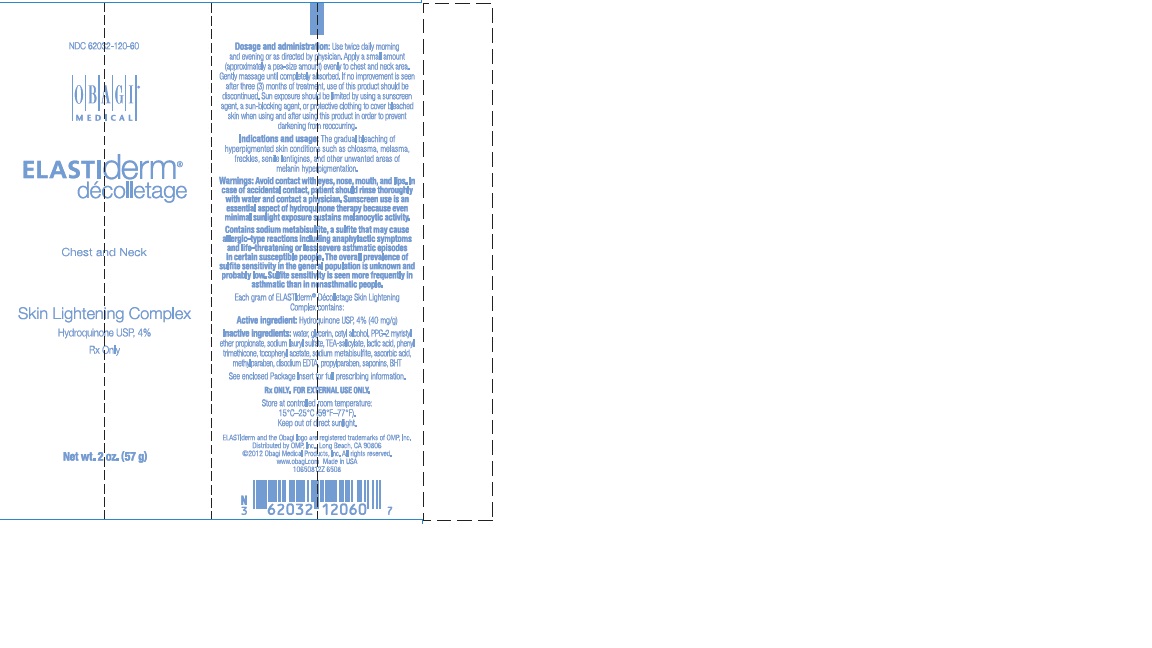 DRUG LABEL: ELASTIDERM DECOLLETAGE SKIN LIGHTENING COMPLEX
NDC: 62032-120 | Form: LOTION
Manufacturer: OMP, INC.
Category: prescription | Type: HUMAN PRESCRIPTION DRUG LABEL
Date: 20140623

ACTIVE INGREDIENTS: HYDROQUINONE 40 mg/1 g
INACTIVE INGREDIENTS: WATER; GLYCERIN; CETYL ALCOHOL; PPG-2 MYRISTYL ETHER PROPIONATE; SODIUM LAURYL SULFATE; TROLAMINE SALICYLATE; LACTIC ACID; PHENYL TRIMETHICONE; .ALPHA.-TOCOPHEROL ACETATE; SODIUM METABISULFITE; ASCORBIC ACID; METHYLPARABEN; EDETATE DISODIUM; PROPYLPARABEN; BUTYLATED HYDROXYTOLUENE

Obagi® Skin Lightening Complex
(Hydroquinone USP, 4%)
Skin Bleaching Cream

Rx Only
FOR EXTERNAL USE ONLY

Each gram of Skin Lightening Complex contains:

Active ingredient:Hydroquinone USP, 4% (40 mg/g)

Inactive ingredients: water, glycerin, cetyl alcohol, PPG-2 myristyl ether propionate, sodium lauryl sulfate, TEA-salicylate, lactic acid, phenyl trimethicone, tocopheryl acetate, sodium metabisulfite, ascorbic acid, methylparaben, disodium EDTA, propylparaben, saponins, BHT

Description:

Hydroquinone is 1,4-benzenediol. The drug is freely soluble in water and in alcohol. Chemically, hydroquinone is designated as p-dihydroxybenzene; the empirical formula is C6H6O2; the molecular weight is 110.11 g/mol. The chemical structure is in the diagram to the right.

Clinical Pharmacology:

Topical application of hydroquinone produces a reversible depigmentation of the skin by inhibition of the enzymatic oxidation of tyrosine to 3, 4-dihydroxyphenylalanine (DOPA) and suppression of other melanocyte metabolic processes.

Exposure to sunlight or ultraviolet light will cause repigmentation of the bleached areas, which may be prevented by the use of sunblocking agents or sunscreen agents.

Indications and Usage:

For the gradual bleaching of hyperpigmented skin conditions such as chloasma, melasma, freckles, senile lentigines, and other unwanted areas of melanin hyperpigmentation.

Contraindications:

People with prior history of sensitivity or allergic reaction to this product or any of its ingredients should not use it. The safety of topical hydroquinone use during pregnancy or in children (12 years and under) has not been established.

Dosage and Administration:

A thin application should be applied once or twice daily or as directed by a physician. If no improvement is seen after three (3) months of treatment, use of this product should be discontinued. Sun exposure should be limited by using a sunscreen agent, a sunblocking agent, or protective clothing to cover bleached skin when using and after using this product in order to prevent darkening from reoccurring.

Warnings:

Hydroquinone is a skin bleaching agent, which may produce unwanted cosmetic effects if not used as directed. The physician should be familiar with the contents of this insert before prescribing or dispensing this medication.

Test for skin sensitivity before using by applying a small amount to an unbroken patch of skin and check within 24 hours. Minor redness is not a contraindication, but where there is itching or vesicle formation or excessive inflammatory response, the product should be discontinued and a physician consulted. Close patient supervision is recommended.

Avoid contact with the eyes, nose, mouth, and lips. In case of accidental contact, the patient should rinse thoroughly with water and contact a physician.

Sunscreen use is an essential aspect of hydroquinone therapy because even minimal sunlight exposure sustains melanocytic activity.

Contains sodium metabisulfite, a sulfite that may cause allergic-type reactions including anaphylactic symptoms and life-threatening or less severe asthmatic episodes in certain susceptible people. The overall prevalence of sulfite sensitivity in the general population is unknown and probably low. Sulfite sensitivity is seen more frequently in asthmatic than in nonasthmatic people.

Precautions:

(also see WARNINGS)

Treatment should be limited to relatively small areas of the body at one time since some patients experience a transient skin reddening and a mild burning sensation, which does not preclude treatment.

Pregnancy Category C:

Animal reproduction studies have not been conducted with topical hydroquinone. It is also not known whether hydroquinone can cause fetal harm when used topically on a pregnant woman or affect reproductive capacity. It is not known to what degree, if any, topical hydroquinone is absorbed systemically. Topical hydroquinone should be used on pregnant women only when clearly indicated.

Nursing Mothers:

It is not known whether topical hydroquinone is absorbed or excreted in human milk. Caution is advised when topical hydroquinone is used by a nursing mother.

Pediatric Usage:

Safety and effectiveness in children below the age of 12 years have not been established.

Adverse Reactions:

No systemic adverse reactions have been reported. Occasional hypersensitivity (localized contact dermatitis) may occur, in which case the product should be discontinued and the physician notified immediately.

How Supplied:

Obagi Skin Lightening Complex is available as follows:

2.0 oz. (57 g) tube
NDC 62032-120-60

STORAGE AND HANDLING

Store at controlled room temperature:
15°C-25°C (59°F-77°F)

OBAGI®
MEDICAL

Obagi is a registered trademark of OMP, Inc.
Distributed by OMP, Inc.
© 2012 Obagi Medical Products, Inc.

All rights reserved.
Long Beach, CA 90806
Made in USA. www.obagi.com
60650612Z 09/12

PRINCIPAL DISPLAY PANEL - 57 g Carton

NDC 62032-120-60

OBAGI®
MEDICAL

ELASTIderm®
décolletage

Chest and Neck

Skin Lightening Complex

Hydroquinone USP, 4%
Rx Only

Net wt. 2 oz. (57 g)